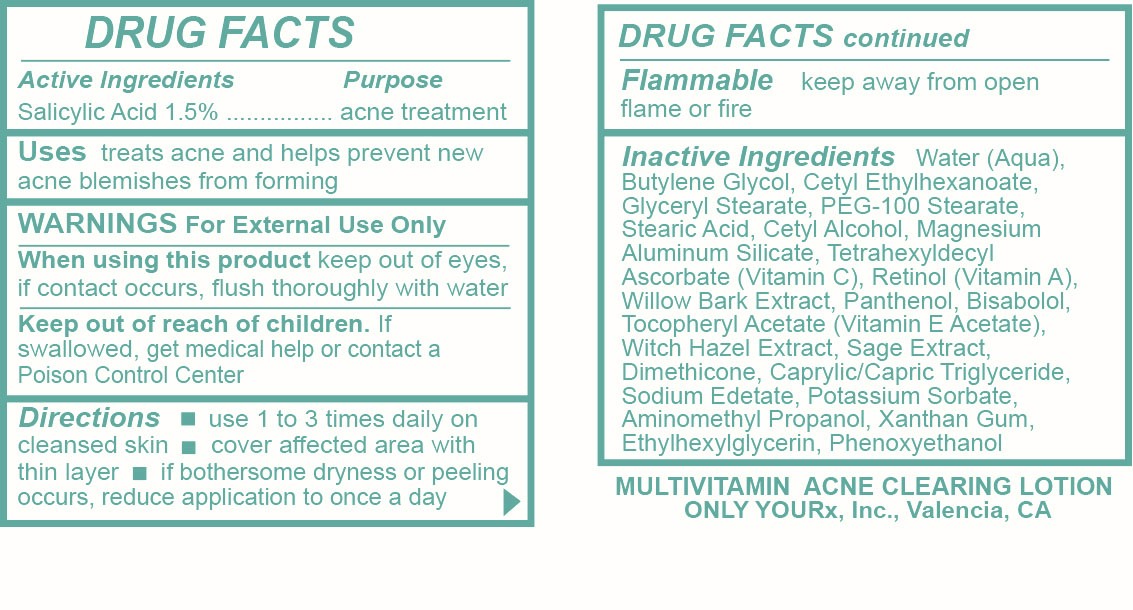 DRUG LABEL: Multi Vitamin Acne Clearing
NDC: 70367-013 | Form: LOTION
Manufacturer: Only Yourx, Inc.
Category: otc | Type: HUMAN OTC DRUG LABEL
Date: 20200123

ACTIVE INGREDIENTS: SALICYLIC ACID 1.5 g/100 mL
INACTIVE INGREDIENTS: COBALT DISODIUM EDETATE; POTASSIUM SORBATE; PHENOXYETHANOL; BUTYLENE GLYCOL; CETYL ETHYLHEXANOATE; GLYCERYL STEARATE SE; PEG-100 STEARATE; STEARIC ACID; CETYL ALCOHOL; MAGNESIUM ALUMINUM SILICATE; TETRAHEXYLDECYL ASCORBATE; RETINOL; WILLOW BARK; PANTHENOL; .ALPHA.-BISABOLOL, (+/-)-; .ALPHA.-TOCOPHEROL ACETATE; WITCH HAZEL; SAGE; DIMETHICONE; CAPRYLIC/CAPRIC/LAURIC TRIGLYCERIDE; AMINOMETHYL PROPANEDIOL; XANTHAN GUM; ETHYLHEXYLGLYCERIN

Active Ingredients: Salicyclic Acid 1.5%

PURPOSE

Treat acne and help prevent new acne blemishes from forming

DOSAGE AND ADMINISTRATION

Use 1 to 3 times daily on cleansed skin; cover affected area with thin layer; if bothersome dryness or peeling occurs, reduce applicatoin to once a day

INDICATIONS AND USAGE

Uses: treats acne and hleps prevent new acne blemishes from forming

WARNINGS

Warnings: For external use only, When using this product keep out of eyes, if contact occurs, flush thoroughly with water

Keep out of reach of children. If swallowed, get medical help or contact a Poison Control Center

INACTIVE INGREDIENT

Water, Butylene Glycol, Cetyl Ethylhexanoate, Glyceryl Stearate, PEG-100 Stearate, Stearic Acid, Cetyl Alcohol, Magnesium Aluminum Silicate, Tetrahexyldecyl Ascorbate (Vitamin C), Retinol (Vitamin A), Willow Bark Extract, Panthenol, Bisabolol, Tocopheryl Acetate (Vitamin E Acetate), Witch Hazel Extract, Sage Extract, Dimethicone, Caprylic/Capric Triglyceride, Sodium Edetate, Potassium Sorbate, Aminomethyl Propanol, Xanthan Gum, Ethylhexylglycerin, Phenoxyethanol